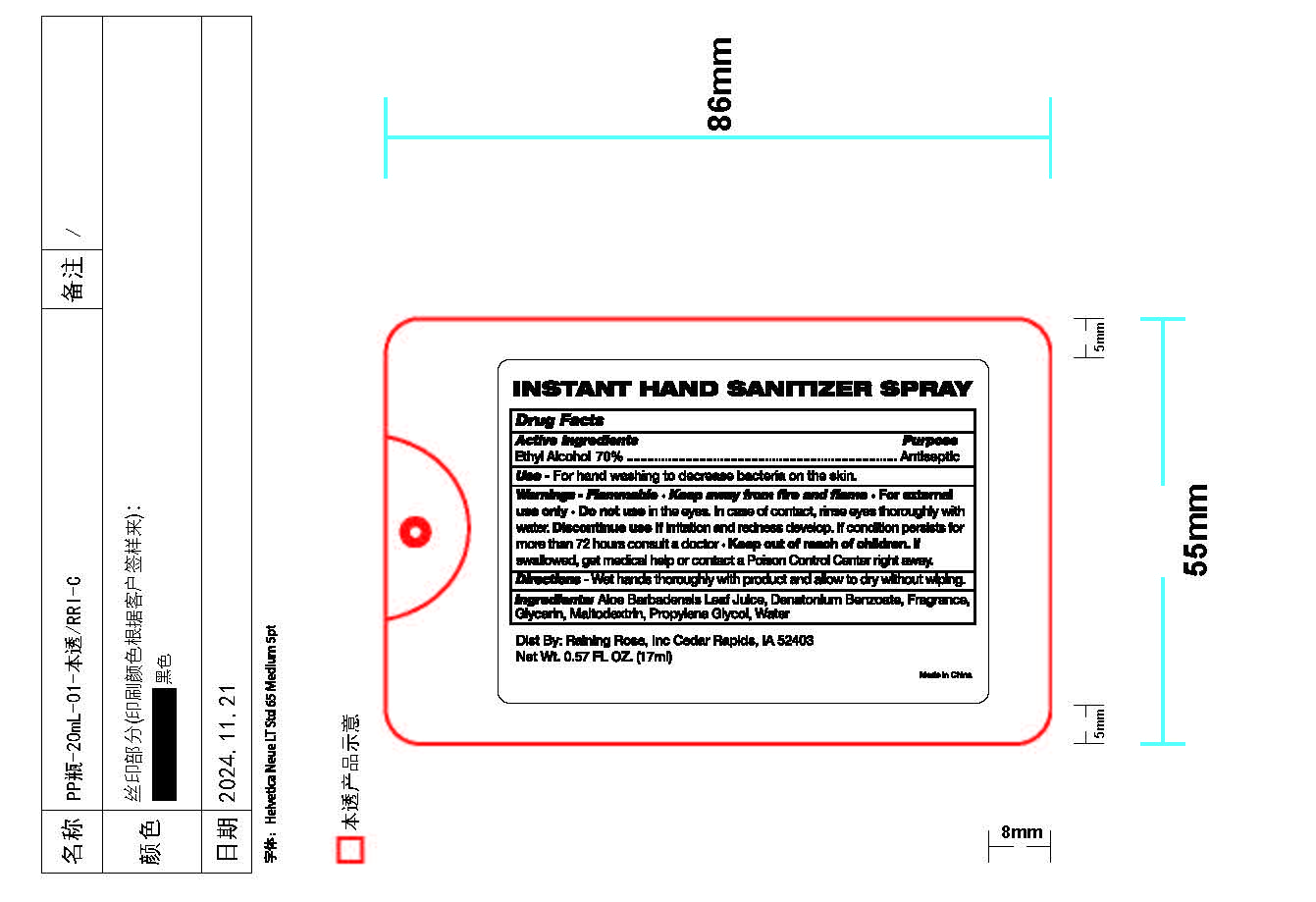 DRUG LABEL: Instant Hand Sanitizer
NDC: 65692-2084 | Form: SPRAY
Manufacturer: Raining Rose, Inc
Category: otc | Type: HUMAN OTC DRUG LABEL
Date: 20250228

ACTIVE INGREDIENTS: ALCOHOL 70 mL/100 mL
INACTIVE INGREDIENTS: MALTODEXTRIN; DENATONIUM BENZOATE; PROPYLENE GLYCOL; GLYCERIN; WATER; ALOE VERA LEAF

ACTIVE INGREDIENT

Ethyl Alcohol 70%

PURPOSE

Antiseptic

INDICATIONS AND USAGE

For hand washing to decrease bacteria on the skin.

Warnings• For external use only
• Flammable, keep away from fire or flame
• Do not use in eyes. In case of contact, rinse eyes thorougly with water.

• Discontinue use if irritation and redness develop.If condition persists for more than 72 hours consult a doctor.

• Keep out of reach of children. If swallowed, get medical help or contact a Poison Control Center right away.

DOSAGE AND ADMINISTRATION

Wet hands thoroughly with product and allow to dry without wiping.

INACTIVE INGREDIENT

Inactive Ingredients: Aloe Barbadensis Leaf Juice, Denatonium Benzoate, Fragrance, Glycerin, Maltodextrin, Propylene Glycol, Water